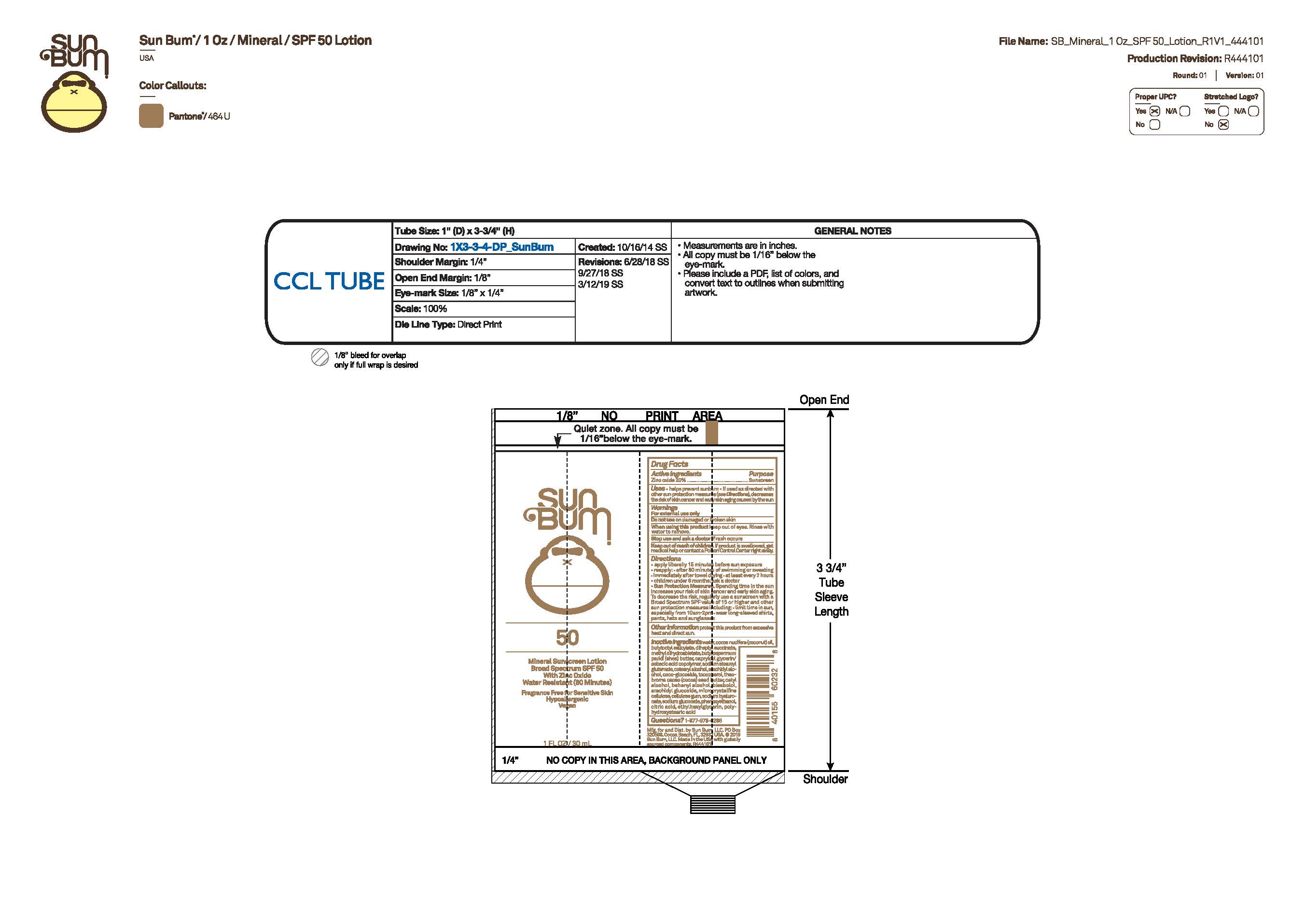 DRUG LABEL: Sun Bum 50 Mineral Sunscreen 1 OZ
NDC: 69039-797 | Form: LOTION
Manufacturer: Sun Bum, LLC
Category: otc | Type: HUMAN OTC DRUG LABEL
Date: 20250813

ACTIVE INGREDIENTS: ZINC OXIDE 200 mg/1 mL
INACTIVE INGREDIENTS: BUTYLOCTYL SALICYLATE; CETEARYL ALCOHOL; TOCOPHEROL; SODIUM GLUCONATE; ETHYLHEXYLGLYCERIN; POLYHYDROXYSTEARIC ACID (2300 MW); SODIUM STEAROYL GLUTAMATE; ARACHIDYL ALCOHOL; COCO-GLUCOSIDE; THEOBROMA CACAO (COCOA) SEED BUTTER; BEHENYL ALCOHOL; CELLULOSE GUM; SODIUM HYALURONATE; CAPRYLOYL GLYCERIN/SEBACIC ACID COPOLYMER (2000 MPA.S); DIHEPTYL SUCCINATE; CETYL ALCOHOL; BISABOLOL; WATER; COCOS NUCIFERA (COCONUT) OIL; METHYL DIHYDROABIETATE; BUTYROSPERMUM PARKII (SHEA) BUTTER; ARACHIDYL GLUCOSIDE; MICROCRYSTALLINE CELLULOSE; PHENOXYETHANOL; CITRIC ACID

Sun Bum 50 Mineral Sunscreen 1 OZ

Active Ingredients

Zinc Oxide 20%

Purpose

Sunscreen

Uses

• helps prevent sunburn • if used as directed with other sun protection measures, (see Directions) decreases the risk of skin cancer and early skin aging caused by the sun

Warnings

For external use only

Do not use on damaged or broken skin

When using this product keep out of eyes. Rinse with water to remove.

Stop use and ask a doctor if rash occurs

Keep out of reach of children. If swallowed, get medical help or contact a Poison Control Center right away.

Warnings

Keep Out Of Reach Of Children

Directions

• apply liberally 15 minutes before sun exposure

• reapply: • after 80 minutes of swimming or sweating • immediately after towel drying • at least every 2 hours

• children under 6 months of age: ask a doctor

• Sun Protection Measures. Spending time in the sun increases your risk of skin cancer and early skin aging. To decrease this risk, regularly use a sunscreen with a Broad Spectrum SPF value of 15 or higher and other sun protection measures including:

• limit time in the sun, especially from 10 a.m.- 2 p.m.

• wear long-sleeved shirts, pants, hats and sunglasses

Directions

• apply liberally 15 minutes before sun exposure

Other Information

protect this product from excessive heat and direct sun

Inactive Ingredients

METHYL DIHYDROABIETATE, TOCOPHEROL, POLYHYDROXYSTEARIC ACID, CITRIC ACID, BUTYROSPERMUM PARKII (SHEA) BUTTER, COCO-GLUCOSIDE, BUTYLOCTYL SALICYLATE, COCOS NUCIFERA (COCONUT) OIL, THEOBROMA CACAO (COCOA) SEED BUTTER, ETHYLHEXYLGLYCERIN, WATER, DIHEPTYL SUCCINATE, CAPRYLOYL GLYCERIN/SEBACIC ACID COPOLYMER, SODIUM STEAROYL GLUTAMATE, CETEARYL ALCOHOL, ARACHIDYL ALCOHOL, CETYL ALCOHOL, BEHENYL ALCOHOL, BISABOLOL, ARACHIDYL GLUCOSIDE, MICROCRYSTALLINE CELLULOSE, CELLULOSE GUM, SODIUM HYALURONATE, SODIUM GLUCONATE, PHENOXYETHANOL

Questions?

1-877-978-6286